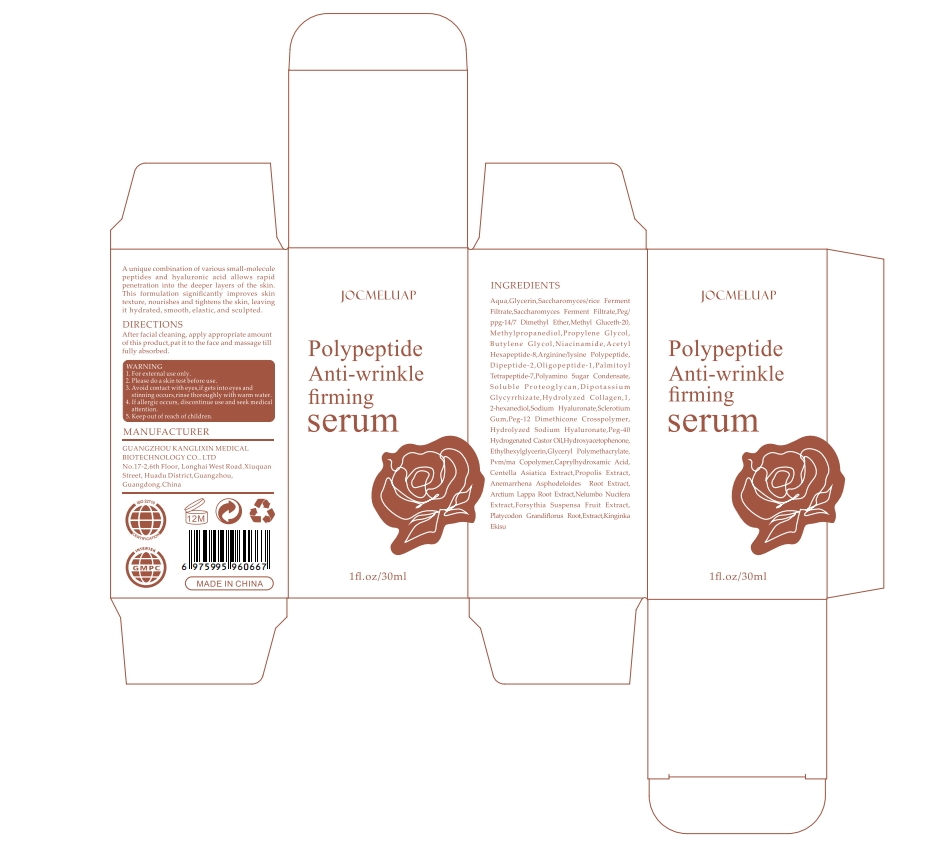 DRUG LABEL: JOCMELUAP
NDC: 84854-005 | Form: LIQUID
Manufacturer: Guangzhou Kanglixin Medical Biotechnology Co., Ltd
Category: otc | Type: HUMAN OTC DRUG LABEL
Date: 20241202

ACTIVE INGREDIENTS: PEG-12 DIMETHICONE/PPG-20 CROSSPOLYMER 0.86 g/0.86 g
INACTIVE INGREDIENTS: DIPROPYLENE GLYCOL; GLYCERIN; SODIUM HYALURONATE; ANEMARRHENA ASPHODELOIDES ROOT; PEG-40 HYDROGENATED CASTOR OIL; SACCHAROMYCES LYSATE; METHYLPROPANEDIOL; BUTYLENE GLYCOL; DIPEPTIDE-2; GRAPEFRUIT OIL; SACCHAROMYCES CEREVISIAE; PEG-8; HYDROXYACETOPHENONE; PROTEOGLYCAN 4; POLYAMINOPROPYL BIGUANIDE HYDROCHLORIDE; ARCTIUM LAPPA ROOT; FORSYTHIA SUSPENSA FRUIT; ETHYLHEXYLGLYCERIN; PVM/MA DECADIENE CROSSPOLYMER (58000 MPA.S); CENTELLA ASIATICA; GLYCERYL POLYMETHACRYLATE (300000 MPA.S); PLATYCODON GRANDIFLORUS ROOT; DIPOTASSIUM GLYCYRRHIZATE; SCLEROTIUM GUM; METHYL GLUCETH-20; PALMITOYL TETRAPEPTIDE-7; PEG/PPG-14/7 DIMETHYL ETHER; NIACINAMIDE; RH-OLIGOPEPTIDE-1; 1,2-HEXANEDIOL; CAPRYLHYDROXAMIC ACID; NELUMBO NUCIFERA ROOT; CETOLETH-20; ACETYL HEXAPEPTIDE-8; ARGININE

Active ingredients

PEG-12 DIMETHICONE CROSSPOLYMER 0.86%

ARGININE 0.01%

ACETYL HEXAPEPTIDE-8 0.1%

Purpose

Face serum

Usage

Improve dry and rough,Reduced facial wrinkles,Facial Contour Firming,Significantly smoother and brighter skin,improves skin elasticity and skin texture.

After facial cleaning, apply appropriate amount
of this product,pat it to the face and massage till
fully absorbed.

Warnings

1. For external use only.
2. Please do a skin test before use.
3. Avoid contact with eyes,if gets into eyes and stinning occurs,rinse thoroughly with warm water.
4. If allergic occurs, discontinue use and seek medical attention.
5. Keep out of reach of children.

Stop use and ask a doctor if

allergic occurs

Do not use

on damaged or broken skin

When using this product

Avoid contact with eyes,,rinse thoroughly with warm water.

Keep out of reach of children.

If swallowed, get medical help or contact a Poison Control Center right away.